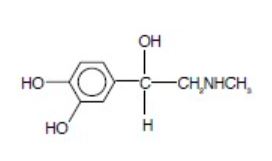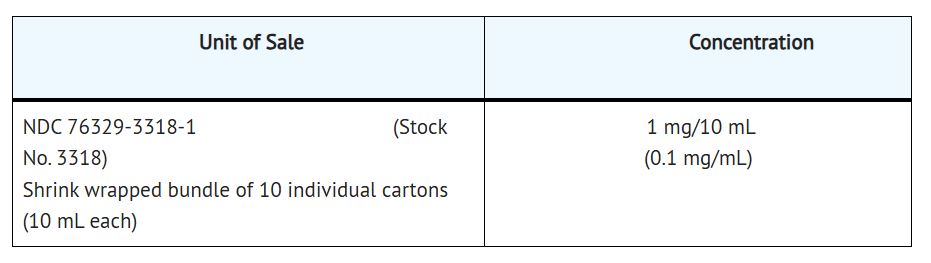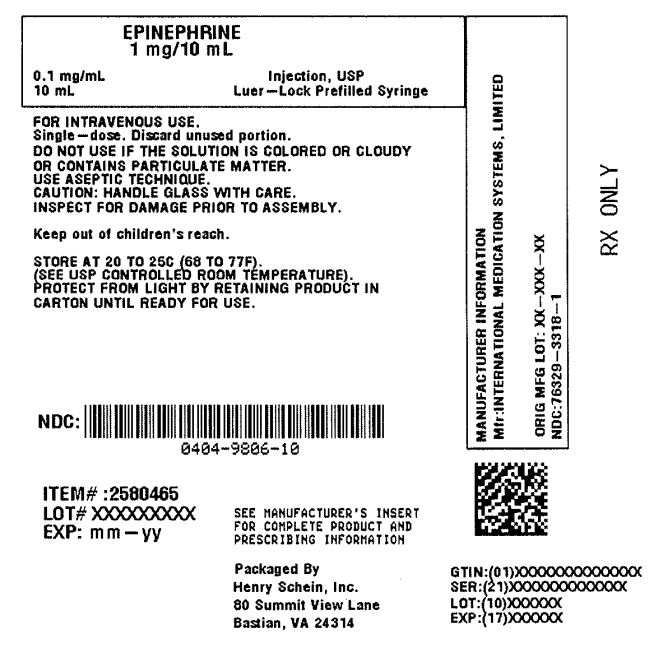 DRUG LABEL: EPINEPHRINE
NDC: 0404-9806 | Form: INJECTION
Manufacturer: Henry Schein, Inc.
Category: prescription | Type: HUMAN PRESCRIPTION DRUG LABEL
Date: 20251031

ACTIVE INGREDIENTS: EPINEPHRINE 0.1 mg/1 mL
INACTIVE INGREDIENTS: CITRIC ACID 3.3 mg/1 mL; EDETATE DISODIUM 0.004 mg/1 mL; SODIUM CHLORIDE 8.2 mg/1 mL; SODIUM CITRATE 1.5 mg/1 mL; SODIUM METABISULFITE; WATER; HYDROCHLORIC ACID; NITROGEN

HIGHLIGHTS OF PRESCRIBING INFORMATION
These highlights do not include all the information needed to use EPINEPHRINE INJECTION USP safely and effectively. See full prescribing information for EPINEPHRINE INJECTION USP.
EPINEPHRINE INJECTION USP, for intravenous use
Initial U.S. Approval: 1939

1 INDICATIONS AND USAGE

Epinephrine is a non-selective alpha and beta adrenergic agonist indicated to increase mean arterial blood pressure in adult patients with hypotension associated with septic shock. (1.1)

2 DOSAGE AND ADMINISTRATION

• Hypotension associated with septic shock (2.2):
o Dilute epinephrine in dextrose solution prior to infusion.
o Infuse epinephrine into a large vein.
o Titrate 0.05 mcg/kg/min to 2 mcg/kg/min to achieve desired blood pressure.
o Wean gradually.

3 DOSAGE FORMS AND STRENGTHS

Injection: 1 mg/10 mL (0.1 mg/mL) single-dose prefilled syringe. (3)

4 CONTRAINDICATIONS

None. (4)

5 WARNINGS AND PRECAUTIONS

• Monitor blood pressure frequently. (5.1)
• Increases cardiac output and causes peripheral vasoconstriction. (5.2)
• May induce cardiac arrhythmias and myocardial ischemia. (5.3)
• Avoid extravasation into tissues, which can cause local necrosis. (5.4)
• Constricts renal blood vessels which may result in oliguria or renal impairment. (5.5)
• Sulfite Warning. (5.6)

6 ADVERSE REACTIONS

Most common adverse reactions to systemically administered epinephrine are headache; anxiety; apprehensiveness; restlessness; tremor; weakness; dizziness; sweating; palpitations; pallor; peripheral coldness; nausea/vomiting; and/or respiratory difficulties. Arrhythmias, including fatal ventricular fibrillation, rapid rises in blood pressure producing cerebral hemorrhage, and angina have occurred. (6.1)

To report SUSPECTED ADVERSE REACTIONS, contact Amphastar Pharmaceuticals, Inc. at 1-800-423-4136 or FDA at 1-800-FDA-1088 or www.fda.gov/medwatch.

7 DRUG INTERACTIONS

- Drugs that counter the pressor effects of epinephrine include alpha blockers, vasodilators such as nitrates, diuretics, antihypertensives, and ergot alkaloids. (7.1)
- Drugs that potentiate the effects of epinephrine include sympathomimetics, beta blockers, tricyclic antidepressants, MAO inhibitors, COMT inhibitors, clonidine, doxapram, oxytocin, levothyroxine sodium, and certain antihistamines. (7.2)
- Drugs that increase the arrhythmogenic potential of epinephrine include beta blockers, cyclopropane and halogenated hydrocarbon anesthetics, quinidine, antihistamines, exogenous thyroid hormones, diuretics, and cardiac glycosides. Observe for development of cardiac arrhythmias. (7.3)
- Potassium-depleting drugs, including corticosteroids, diuretics, and theophylline, potentiate the hypokalemic effects of epinephrine. (7.4)

8 USE IN SPECIFIC POPULATIONS

• Pregnancy: May lead to fetal harm (8.1)
• Elderly patients and pregnant women may be at greater risk of developing adverse reactions when epinephrine is administered parenterally.
(8.1, 8.5)

Revised: 08/2022

FULL PRESCRIBING INFORMATION

1 INDICATIONS AND USAGE

1.1 Hypotension associated with Septic Shock

Epinephrine Injection USP, 1 mg/10 mL (0.1 mg/mL) is indicated to increase mean arterial blood pressure in adult patients with hypotension associated with septic shock.

2 DOSAGE AND ADMINISTRATION

2.1 General Considerations

Inspect visually for particulate matter and discoloration prior to administration, whenever solution and container permit. Do not use if the solution is colored or cloudy, or if it contains particulate matter. Discard any unused portion.

2.2 Hypotension associated with Septic Shock

Dilute epinephrine in 5% Dextrose Injection, USP or 5% Dextrose and Sodium Chloride solution. These dextrose containing fluids provide protection against significant loss of potency by oxidation. Administration in saline solution alone is not recommended. If indicated, administer whole blood or plasma separately.
Add the entire contents of epinephrine prefilled syringe to 1000 mL of a 5% Dextrose containing solution. Each mL of this dilution contains 1 mcg of epinephrine.
Whenever possible, give infusions of epinephrine into a large vein. Avoid using a catheter tie-in technique, because the obstruction to blood flow around the tubing may cause stasis and increased local concentration of the drug. Avoid the veins of the leg in elderly patients or in those suffering from occlusive vascular diseases.
To provide hemodynamic support in septic shock associated hypotension in adult patients, the suggested dosing infusion rate of intravenously administered epinephrine is 0.05 mcg/kg/min to 2 mcg/kg/min, and is titrated to achieve a desired mean arterial pressure (MAP). The dosage may be adjusted periodically, such as every 10 to 15 minutes, in increments of 0.05 mcg/kg/min to 0.2 mcg/kg/min, to achieve the desired blood pressure goal.
After hemodynamic stabilization, wean incrementally over time, such as by decreasing doses of epinephrine every 30 minutes over a 12- to 24-hour period.

3 DOSAGE FORMS AND STRENGTHS

Injection: 10 mL single-dose prefilled syringe containing 1 mg/10 mL (0.1 mg/mL) epinephrine as the hydrochloride in a sterile, clear and colorless solution.

4 CONTRAINDICATIONS

None.

5 WARNINGS AND PRECAUTIONS

5.1 Hypertension

Because individual response to epinephrine may vary significantly, monitor blood pressure frequently and titrate to avoid excessive increases in blood pressure.
Patients receiving monoamine oxidase inhibitors (MAOI) or antidepressants of triptyline or imipramine types may experience severe, prolonged hypertension when given epinephrine.

5.2 Pulmonary Edema

Epinephrine increases cardiac output and causes peripheral vasoconstriction, which may result in pulmonary edema.

5.3 Cardiac Arrhythmias and Ischemia

Epinephrine may induce cardiac arrhythmias and myocardial ischemia in patients, especially patients suffering from coronary artery disease or cardiomyopathy [see Adverse Reactions (6) and Drug Interactions (7.3)].

5.4 Extravasation and Tissue Necrosis with Intravenous Infusion

Avoid extravasation of epinephrine into the tissues, to prevent local necrosis. When Epinephrine Injection is administered intravenously, check the infusion site frequently for free flow. Blanching along the course of the infused vein, sometimes without obvious extravasation, may be attributed to vasa vasorum constriction with increased permeability of the vein wall, permitting some leakage. This also may progress on rare occasions to superficial slough. Hence, if blanching occurs, consider changing the infusion site at intervals to allow the effects of local vasoconstriction to subside.
There is a potential for gangrene in a lower extremity when infusions of catecholamine are given in an ankle vein.
Antidote for Extravasation Ischemia: To prevent sloughing and necrosis in areas in which extravasation has taken place, infiltrate the area with 10 mL to 15 mL of saline solution containing from 5 mg to 10 mg of phentolamine, an adrenergic blocking agent. Use a syringe with a fine hypodermic needle, with the solution being infiltrated liberally throughout the area, which is easily identified by its cold, hard, and pallid appearance. Sympathetic blockade with phentolamine causes immediate and conspicuous local hyperemic changes if the area is infiltrated with 12 hours.

5.5 Renal Impairment

Epinephrine constricts renal blood vessels, which may result in oliguria or renal impairment.

5.6 Allergic Reactions Associated with Sulfite

Contains sodium bisulfite, which may cause mild to severe allergic reactions including anaphylaxis orasthmatic episodes, particularly in patients with a history of allergies. The presence of sodium bisulfite in this product should not preclude its use for the treatment of hypotension associated with septic shock, even if the patient is sulfite-sensitive, as the alternatives to using epinephrine in a life-threatening situation may not be satisfactory. In susceptible patients, consider using a formulation of epinephrine or another vasoconstrictor that does not contain sodium bisulfite.

6 ADVERSE REACTIONS

The following adverse reactions are discussed elsewhere in labeling:
• Hypertension [see Warnings and Precautions (5.1)]
• Pulmonary Edema [see Warnings and Precautions (5.2)]
• Cardiac Arrhythmias and Ischemia [see Warnings and Precautions (5.3)]
• Extravassation and Tissue Necrosis with Intravenous Infusion [see Warnings and Precautions (5.4)]
• Renal Impairment [see Warnings and Precautions (5.5)]
• Allergic Reactions associated with Sulfite [see Warnings and Precautions (5.6)]
The following adverse reactions associated with the infusion of epinephrine were identified in the literature. Because these reactions are reported voluntarily from a population of uncertain size, it is not always possible to estimate their frequency reliably or to establish a causal relationship to drug exposure.
Cardiovascular disorders: tachycardia, supraventricular tachycardia, ventricular arrhythmias, myocardial ischemia, myocardial infarction, limb ischemia, pulmonary edema
Gastrointestinal disorders: Nausea, vomiting
General disorders and administrative site conditions: Chest pain, extravasation
Metabolic: hypoglycemia, hyperglycemia, insulin resistance, hypokalemia, lactic acidosis
Nervous system disorders: Headache, nervousness, paresthesia, tremor, stroke, central nervous system bleeding
Psychiatric disorders: Excitability
Renal disorders: Renal insufficiency
Respiratory: Pulmonary edema, rales
Skin and subcutaneous tissue disorders: Diaphoresis, pallor, piloerection, skin blanching, skin necrosis with extravasation

7 DRUG INTERACTIONS

7.1 Drugs Antagonizing Pressor Effects of Epinephrine

• α-blockers, such as phentolamine
• Vasodilators, such as nitrates
• Diuretics
• Antihypertensives
• Ergot alkaloids
• Phenothiazine antipsychotics

7.2 Drugs Potentiating Pressor Effects of Epinephrine

• Sympathomimetics
• β-blockers, such as propranolol
• Tricyclic anti-depressants
• Monoamine oxidase (MAO) inhibitors
• Catechol-O-methyl transferase (COMT) inhibitors, such as entacapon
• Clonidine
• Doxapram
• Oxytocin

7.3 Drugs Potentiating Arrhythmogenic Effects of Epinephrine

Patients who are concomitantly receiving any of the following drugs should be observed carefully for the development of cardiac arrhythmias [see Warnings and Precautions (5.6) and Adverse Reactions (6)].
• β-blockers, such as propranolol
• Cyclopropane or halogenated hydrocarbon anesthetics, such as halothane
• Antihistamines
• Thyroid hormones
• Diuretics
• Cardiac glycosides, such as digitalis glycosides
• Quinidine

7.4 Drugs Potentiating Hypokalemic Effects of Epinephrine

• Potassium depleting diuretics
• Corticosteroids
• Theophylline

8 USE IN SPECIFIC POPULATIONS

8.1 Pregnancy

Risk Summary

Limited published data on epinephrine use in pregnant women are not sufficient to determine a drug-associated risk for major birth defects or miscarriage. However, there are risks to the mother and fetus associated with epinephrine use during labor or delivery, and risks due to untreated hypotension associated with septic shock (see Clinical Considerations). In animal reproduction studies, epinephrine demostrated adverse developmental effects when administed to pregnant rabbits (gastroschisis), mice (teratogenie effects, embryonic lethality, and delayed skeletal ossification), and hamsters (embryonic lethality and delayed skeletal ossification) during organogenesis at doses approximately 15 times, 3 times and 2 times, respectively, the maximum recommended daily intramuscular or subcutaneous dose (see Data).
The estimated background risk of major birth defects and miscarriage for the indicated population is unknown. All pregnancies have a background risk of birth defect, loss, or other adverse outcomes. In the United States general population, the estimated background risk of major birth defects and miscarriage in clinically recognized pregnancies is 2 to 4% and 15 to 20%, respectively.

Clinical Considerations

Hypotension associated with septic shock is a medical emergency in pregnancy which can be fatal if left untreated. Delaying treatment in pregnant women with hypotension associated with septic shock may increase the risk of maternal and fetal morbidity and mortality. Do not withhold life-sustaining therapy for a pregnant woman.

Labor or Delivery
Epinephrine usually inhibits spontaneous or oxytocin-induced contractions of the pregnant human uterus and may delay the second stage of labor. Avoid epinephrine during the second stage of labor. In dosage sufficient to reduce uterine contractions, the drug may cause a prolonged period of uterine atony with hemorrhage. Avoid epinephrine in obstetrics when maternal blood pressure exceeds 130/80 mmHg.
Although epinephrine may improve maternal hypotension associated with septic shock and anaphylaxis, it may result in uterine vasoconstriction, decreased uterine blood flow, and fetal anoxia.

Data

Animal Data
In an embryofetal development study with pregnant rabbits dosed during the period of organogenesis (on days 3 to 5, 6 to 7, or 7 to 9 of gestation), epinephrine caused teratogenic effects (including gastroschisis) at doses approximately 15 times the maximum recommended intramuscular, subcutaneous, or intravenous dose (on a mg/m2 basis at a maternal subcutaneous dose of 1.2 mg/kg/day for 2 to 3 days).Animals treated on days 6 to 7 had decreased number of implantations.
In an embryofetal development study, pregnant mice were administered epinephrine (0.1 to 10 mg/kg/day) on Gestation Days 6 to 15. Teratogenic effects, embryonic lethality, and delays in skeletal ossification were observed at approximately 3 times the maximum recommended intramuscular, subcutaneous, or intravenous dose (on a mg/m2 basis at maternal subcutaneous dose of 1 mg/kg/day for 10 days). These effects were not seen in mice at approximately 2 times the maximum recommended daily intramuscular or subcutaneous dose (on a mg/m2 basis at a subcutaneous maternal dose of 0.5 mg/kg/day for 10 days).
In an embryofetal development study with pregnant hamsters dosed during the period of organogenesis from gestation days 7 to 10, epinephrine produced reductions in litter size and delayed skeletal ossification at doses approximately 2 times the maximum recommended intramuscular, subcutaneous, or intravenous dose (on a mg/m2 basis at a maternal subcutaneous dose of 0.5 mg/kg/day).

8.2 Lactation

Risk Summary

There is no information regarding the presence of epinephrine in human milk or the effects of epinephrine on the breastfed infant or on milk production. However, due to its poor oral bioavailability and short half-life, epinephrine exposure is expected to be very low in the breastfed infant. The lack of clinical data during lactation precludes a clear determination of the risk of epinephrine to a breastfed infant.

8.4 Pediatric Use

Safety and effectiveness of epinephrine in pediatric patients with septic shock have not been established.

8.5 Geriatric Use

Clinical studies of epinephrine for the treatment of hypotension associated with septic shock did not include sufficient numbers of subjects aged 65 and over to determine whether they respond differently from younger subjects. Other reported clinical experience has not identified differences in responses between the elderly and younger patients. In general, dose selection for an elderly patient should be cautious, usually starting at the low end of the dosing range, reflecting the greater frequency of decreased hepatic, renal, or cardiac function, and of concomitant disease or other drug therapy.

10 OVERDOSAGE

Overdosage of epinephrine may produce extremely elevated arterial pressure, which may result in cerebrovascular hemorrhage, particularly in elderly patients. Overdosage may also result in pulmonary edema because of peripheral vascular constriction together with cardiac stimulation. Epinephrine overdosage may also cause transient bradycardia followed by tachycardia and these may be accompanied by potentially fatal cardiac arrhythmias. Premature ventricular contractions may appear within one minute after injection and may be followed by multifocal ventricular tachycardia (prefibrillation rhythm). Subsidence of the ventricular effects may be followed by atrial tachycardia and occasionally by atrioventricular block. Myocardial ischemia and infarction, cardiomyopathy, extreme pallor and coldness of the skin, metabolic acidosis due to elevated blood lactic acid levels, and renal insufficiency and failure have also been reported.
Epinephrine is rapidly inactivated in the body and treatment following overdose is primarily supportive. Treatment of pulmonary edema consists of a rapidly acting alpha-adrenergic blocking drug (such as phentolamine mesylate) and respiratory support. Treatment of arrhythmias consists of administration of a beta-adrenergic blocking drug (such as propranolol). If necessary, pressor effects may be counteracted by rapidly acting vasodilators (such as nitrites) or alpha-adrenergic blocking drugs. If prolonged hypotension follows such measures, it may be necessary to administer another pressor drug.

11 DESCRIPTION

Epinephrine, USP is a non-selective alpha and beta-adrenergic agonist designated chemically as (R)-4-(1-Hydroxy-2-(methylamino)ethyl)benzene-1,2-diol, a white, microcrystalline powder. It has the following structural formula:

The molecular weight of epinephrine is 183.2.

Epinephrine solution deteriorates rapidly on exposure to air or light, turning pink from oxidation to adrenochrome and brown from the formation of melanin.
Epinephrine Injection USP, 1 mg/10 mL (0.1 mg/mL) is supplied as a sterile aqueous solution that is clear, colorless and nonpyrogenic. Each mL of the solution contains epinephrine (0.1 mg) as the active ingredient and the following inactive ingredients: citric acid monohydrate (3.3 mg), edetate disodium dihydrate (0.004 mg), sodium chloride (8.2 mg), sodium citrate dihydrate (1.5 mg), sodium metabisulfite, and Water for Injection. Hydrochloric acid solution is added to dissolve the active ingredient. Sodium hydroxide solution is added to adjust the pH. Nitrogen is used for blanketing protection.
Solution must be diluted prior to intravenous use.

12 CLINICAL PHARMACOLOGY

12.1 Mechanism of Action

Epinephrine acts on both alpha (α)- and beta (β)-adrenergic receptors. The mechanism of the rise in blood pressure is 3-fold: a direct myocardial stimulation that increases the strength of ventricular contraction (positive inotropic action), an increased heart rate (positive chronotropic action), and peripheral vasoconstriction.

12.2 Pharmacodynamics

Intravenous use for hypotension associated with septic shock
Following intravenous administration of epinephrine, increases in systolic blood pressure and heart rate are observed. Decreases in systemic vascular resistance and diastolic blood pressure are observed at low doses of epinephrine because of β2-mediated vasodilation, but are overtaken by α1-mediated peripheral vasoconstriction at higher doses leading to increase in diastolic blood pressure. The onset of blood pressure increase following an intravenous dose of epinephrine is < 5 minutes and the time to offset blood pressure response occurs within 20 min. Most vascular beds are constricted including renal, splanchnic, mucosal and skin.

12.3 Pharmacokinetics

Following intravenous injection, epinephrine is rapidly cleared from the plasma with an effective half-life of < 5 min. A pharmacokinetic steady state following continuous intravenous infusion is achieved within 10-15 min. In patients with septic shock, epinephrine displays dose-proportional pharmacokinetics in the infusion dose range of 0.03 to 1.7 mcg/kg/min.
Epinephrine is extensively metabolized with only a small amount excreted unchanged.
Epinephrine is rapidly degraded to vanillylmandelic acid, an inactive metabolite, by monoamine oxidase and catechol-O-methyltransferase that are abundantly expressed in the liver, kidneys and other extraneuronal tissues. The tissues with the highest contribution to removal of circulating exogenous epinephrine are the liver (32%), kidneys (25%), skeletal muscle (20%), and mesenteric organs (12%).

Specific Populations
Elderly
In a pharmacokinetic study of 45-minute epinephrine infusions given to healthy men aged 20 to 25 years and healthy men aged 60 to 65 years, the mean plasma metabolic clearance rate of epinephrine at steady state was greater among the older men (144.8 versus 78 mL/kg/min for a 14.3 ng/kg/min infusion).

Body Weight
Body weight has been found to influence epinephrine pharmacokinetics. Higher body weight was associated with a higher plasma epinephrine clearance and a lower concentration plateau.

13 NONCLINICAL TOXICOLOGY

13.1 Carcinogenesis, Mutagenesis, Impairment of Fertility

Long-term studies to evaluate the carcinogenic potential of epinephrine have not been conducted.
Epinephrine and other catecholamines have been shown to have mutagenic potential in vitro. Epinephrine was positive in the Salmonella bacterial reverse mutation assay, positive in the mouse lymphoma assay, and negative in the in vivo micronucleus assay. Epinephrine is an oxidative mutagen based on the E. coli WP2 Mutoxitest bacterial reverse mutation assay. This should not prevent the use of epinephrine under the conditions noted under the Indications and Usage.
The potential for epinephrine to impair reproductive performance has not been evaluated, but epinephrine has been shown to decrease implantation in female rabbits dosed subcutaneously with 1.2 mg/kg/day (15-fold the highest human intramuscular or subcutaneous daily dose) during gestation days 3 to 9.

13.2 Animal Toxicology and/or Pharmacology

Epinephrine was associated with metabolic effects, decreased mesentery, coronary and renal conductance in a sheep model of septic shock. Data from hemolysis study have shown that epinephrine at 1:1000 dilution is non-hemolytic. Epinephrine infusion significantly increased the MAP (69 vs. 86 mmHg) and cardiac output (6.4 vs. 7.1 L/min) and decreased renal blood flow (330 vs. 247 mL/min).

14 CLINICAL STUDIES

14.1 Hypotension associated with Septic Shock

Fourteen clinical studies from the literature documented that epinephrine increases the mean arterial pressure (MAP) in patients with hypotension associated with septic shock.

16 HOW SUPPLIED/STORAGE AND HANDLING

Epinephrine Injection USP, 1 mg/10 mL (0.1 mg/mL) is a clear colorless solution available in a single-dose Luer-Jet Luer-Lock prefilled syringe packaged in a carton.
It is supplied in the following presentation.

Epinephrine is light sensitive. Protect from light until ready to use.
Do not refrigerate. Protect from freezing.
Store at room temperature, between 20° to 25°C (68° to 77°F). (See USP Controlled Room Temperature.) Protect from alkalis and oxidizing agents.

Product repackaged by: Henry Schein, Inc., Bastian, VA 24314
From Original Manufacturer/Distributor's NDC and Unit of Sale | To Henry Schein Repackaged Product NDC and Unit of Sale | Total Strength/Total Volume (Concentration) per unit
NDC 76329-3318-1 Shrink wrapped bundle of 10 individual cartons | NDC 0404-9806-10 1 10 mL Syringe in a bag (Syringe bears NDC 76329-3318-1) | 1 mg/10 mL (0.1 mg/mL)

Rx Only

Manufactured by:
INTERNATIONAL MEDICATION SYSTEMS, LIMITED
So. EL MONTE, CA 91733, U.S.A.
An Amphastar Pharmaceuticals Company
©INTERNATIONAL MEDICATION SYSTEMS, LIMITED 2022

REV 08/22